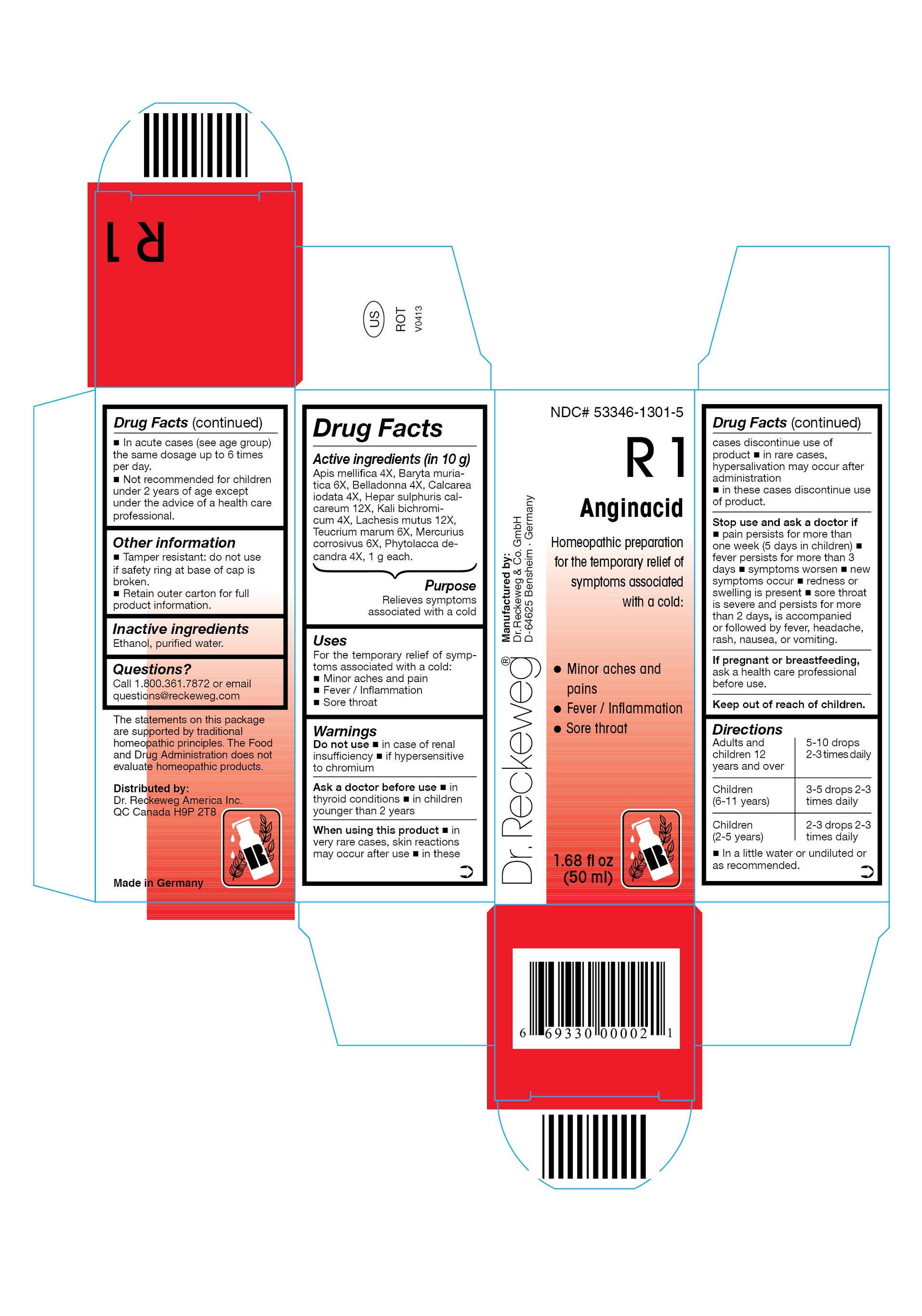 DRUG LABEL: DR. RECKEWEG R1 Anginacid
NDC: 53346-1301 | Form: LIQUID
Manufacturer: PHARMAZEUTISCHE FABRIK DR. RECKEWEG & CO
Category: homeopathic | Type: HUMAN OTC DRUG LABEL
Date: 20130409

ACTIVE INGREDIENTS: APIS MELLIFERA 4 [hp_X]/50 mL; BARIUM CHLORIDE DIHYDRATE 6 [hp_X]/50 mL; ATROPA BELLADONNA 4 [hp_X]/50 mL; CALCIUM IODIDE 4 [hp_X]/50 mL; CALCIUM SULFIDE 12 [hp_X]/50 mL; POTASSIUM DICHROMATE 4 [hp_X]/50 mL; LACHESIS MUTA VENOM 12 [hp_X]/50 mL; TEUCRIUM MARUM 6 [hp_X]/50 mL; MERCURIC CHLORIDE 6 [hp_X]/50 mL; PHYTOLACCA AMERICANA ROOT 4 [hp_X]/50 mL
INACTIVE INGREDIENTS: ALCOHOL; WATER

DR. RECKEWEG R1 Anginacid

Active ingredients

Apis mellifica 4X, Baryta muriatica 6X, Belladonna 4X, Calcarea iodata 4X, Hepar sulphuris calcareum 12X, Kali bichromicum 4X, Lachesis mutus 12X, Teucrium marum 6X, Mercurius corrosivus 6X, Phytolacca decandra 4X, 1 g each in 10 g.

Purpose

Relieves symptoms associated with a cold

Uses

For the temporary relief of symptoms associated with a cold:

- Minor aches and pains
- Fever / Inflammation
- Sore throat

Warnings

Do not use

- in case of renal insufficiency
- if hypersensitive to chromium

Ask a doctor before use

- in thyroid conditions
- in children younger than 2 years

When using this product

- In very rare cases, skin reactions may occur after use.
- In these cases discontinue use of product.
- In rare cases, hypersalivation may occur after administration.
- In these cases discontinue use of product.

Stop use and ask a doctor if

- pain persists for more than one week (5 days in children)
- fever persists for more than 3 days
- symptoms worsen
- new symptoms occur
- redness or swelling is present
- sore throat is severe and persists for more than 2 days, is accompanied or followed by fever, headache, rash, nausea, or vomiting

PREGNANCY OR BREAST FEEDING

If pregnant or breastfeeding, ask a health care professional before use.

Keep out of reach of children.

Directions

Adults and children ≥ 12 years 5-10 drops; children (6-11 years) 3-5 drops;

children (2-5 years) 2-3 drops, all ages take 2-3 times daily in a little water or undiluted or as recommended.

In acute cases (see age group) the same dosage up to 6 times per day.

Not recommended for children under 2 years of age except under the advice of a health care professional.

Other information

- Tamper resistant: do not use if safety ring at base of cap is broken.
- Retain outer carton for full product information.

Inactive ingredients
Ethanol, purified water.

Questions?

Call 1-800-361-7872 or email questions@reckeweg.com

PACKAGE LABEL

NDC# 53346-1301-5

Dr. Reckeweg R1 Anginacid

Homeopathic preparation for the temporary relief of symptoms associated with a cold:

* Minor aches and pains

* Fever / Inflammation

* Sore throat

Manufactured by:

Dr. Reckeweg Co. GmbH

D-64625 Bensheim

Germany

1.68 fl oz

(50 ml)